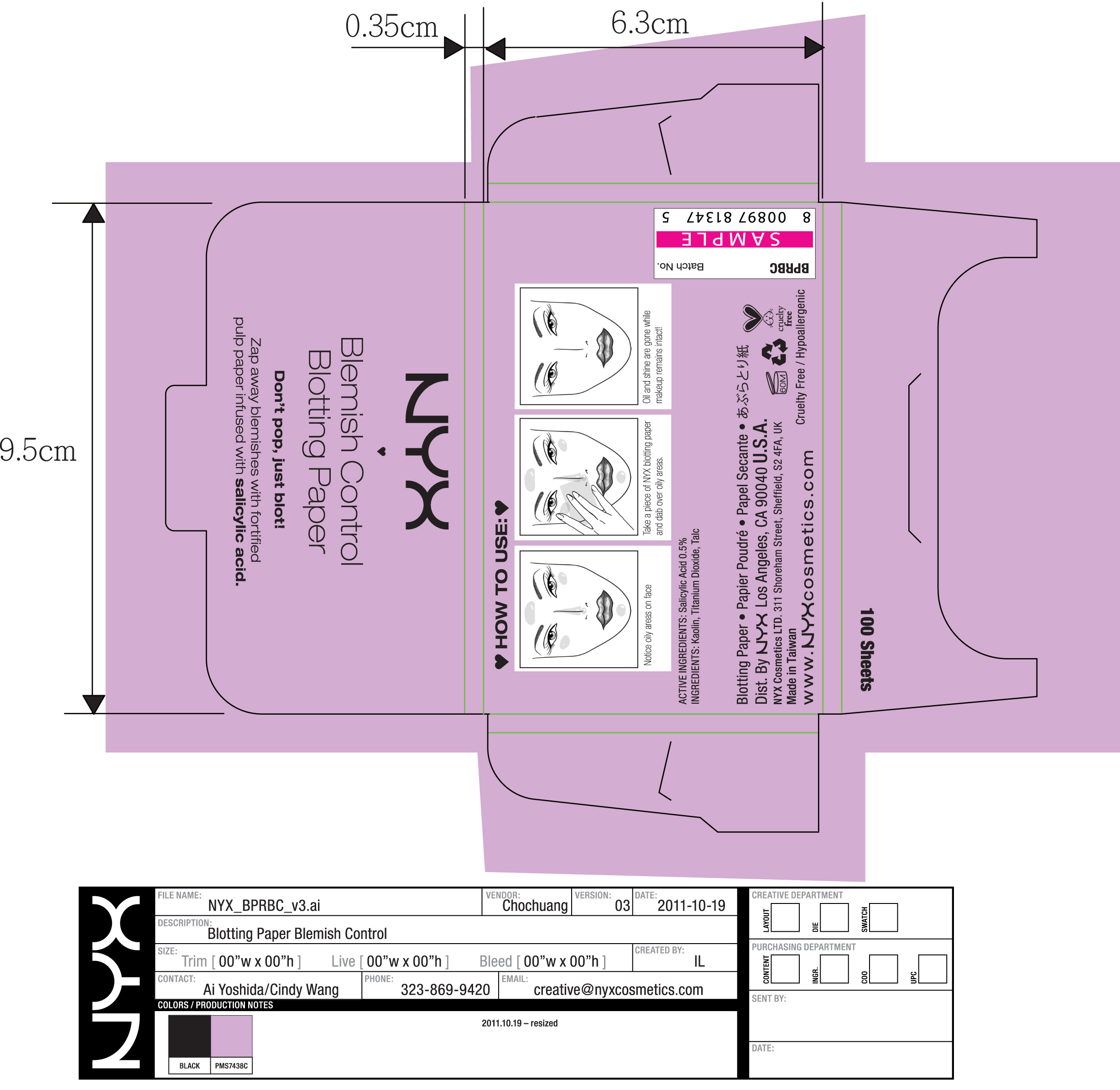 DRUG LABEL: Blemish Control Blotting Paper
NDC: 76449-050 | Form: STRIP
Manufacturer: NYX Los Angeles Inc.
Category: otc | Type: HUMAN OTC DRUG LABEL
Date: 20111021

ACTIVE INGREDIENTS: Salicylic Acid 0.03 mg/1 1
INACTIVE INGREDIENTS: Kaolin; Titanium Dioxide; Talc

Blemish Control Blotting Paper

ACTIVE INGREDIENTS: Salicylic Acid 0.5%

INACTIVE INGREDIENT

INGREDIENTS: Kaolin, Titanium Dioxide, Talc

PURPOSE

Blemish Control

Keep Out Of Reach Of Children

WARNINGS

For External Use Only

Keep Out Of Eyes

INDICATIONS AND USAGE

Take a piece of NYX Blotting Paper and dab over oily areas